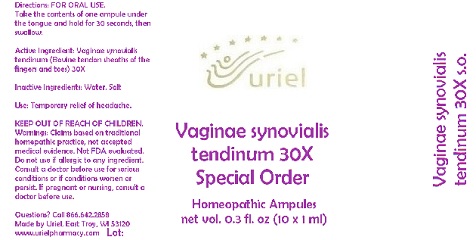 DRUG LABEL: Vaginae synovialis tendinum 30 Special Order
NDC: 48951-9300 | Form: LIQUID
Manufacturer: Uriel Pharmacy Inc.
Category: homeopathic | Type: HUMAN OTC DRUG LABEL
Date: 20180509

ACTIVE INGREDIENTS: BOS TAURUS TENDON 30 [hp_X]/1 mL
INACTIVE INGREDIENTS: SODIUM CHLORIDE; WATER

Vaginae synovialis tendinum 30 Special Order

INDICATIONS AND USAGE

Directions: FOR ORAL USE.

DOSAGE AND ADMINISTRATION

Take the contents of one ampule under the tongue and hold for 30 seconds, then swallow.

Active Ingredient: Vaginae synovialis tendinum (Bovine tendon sheaths of the fingers and toes) 30X

Inactive Ingredients: Water, Salt

PURPOSE

Use: Temporary relief of headache.

KEEP OUT OF REACH OF CHILDREN.

WARNINGS

Warnings: Claims based on traditional homepathic practice, not accepted medical evidence. Not FDA evaluated. Do not use if allergic to any ingredient. Consult a doctor before use for serious conditions or if conditions worsen or persist. If pregnant or nursing, consult a doctor before use.

Questions? Call 866.642.2858
Made by Uriel, East Troy, WI 53120
www.urielpharmacy.com